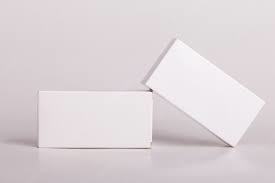 DRUG LABEL: Truemed Group LLC
NDC: 82922-032 | Form: INHALANT
Manufacturer: Truemed Group LLC
Category: prescription | Type: HUMAN PRESCRIPTION DRUG LABEL
Date: 20220811

ACTIVE INGREDIENTS: SALBUTAMON 0.5 g/10 mL

SALBUTAMOL SULFATE